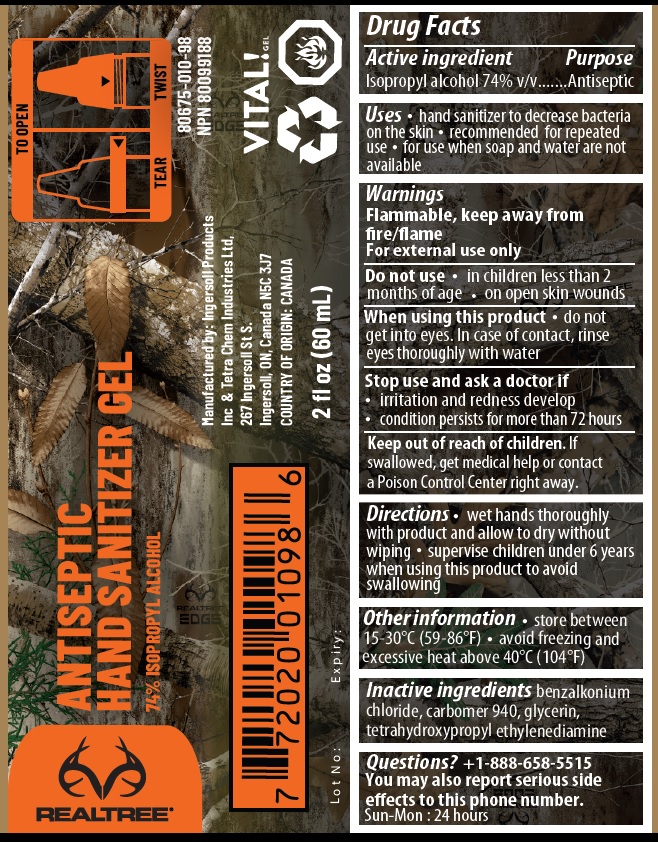 DRUG LABEL: VITAL Gel ANTISEPTIC HAND SANITIZER
NDC: 80675-010 | Form: GEL
Manufacturer: Ingersoll Products Inc
Category: otc | Type: HUMAN OTC DRUG LABEL
Date: 20201111

ACTIVE INGREDIENTS: ISOPROPYL ALCOHOL 74 mL/100 mL
INACTIVE INGREDIENTS: BENZALKONIUM CHLORIDE; CARBOMER HOMOPOLYMER TYPE C (ALLYL PENTAERYTHRITOL CROSSLINKED); GLYCERIN; EDETOL

VITAL Gel ANTISEPTIC HAND SANITIZER

Active ingredient

Isopropyl alcohol 74% v/v

Purpose

Antiseptic

Uses

• hand sanitizer to decrease bacteria on the skin • recommended for repeated use • for use when soap and water are not available

Warnings

Flammable, keep away from fire/flame
For external use only

Do not use • in children less than 2 months of age • on open skin wounds

When using this product • do not get into eyes. In case of contact, rinse eyes thoroughly with water

Stop use and ask a doctor if

- irritation and redness develop
- condition persists for more than 7 2 hours

Keep out of reach of children. If swallowed, get medical help or contact a Poison Control Center right away.

Directions

• wet hands thoroughly with product and allow to dry without wiping • supervise children under 6 years when using this product to avoid swallowing

Other information

• store between 15-30°C (59-86°F) • avoid freezing and excessive heat above 40°C (104°F)

Inactive ingredients

benzalkonium chloride, carbomer 940, glycerin, tetrahydroxypropyl ethylenediamine

Questions? +1-888-658-5515

You may also report serious side effects to this phone number.

Sun-Mon: 24 hours